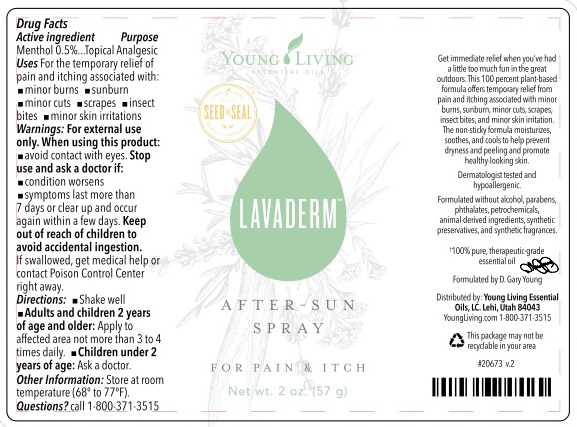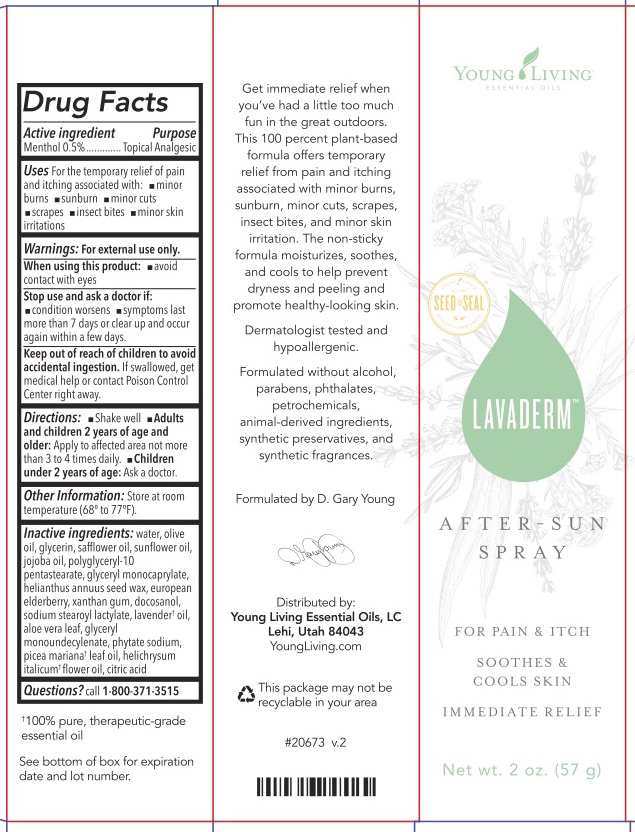 DRUG LABEL: Lavaderm After Sun
NDC: 70631-034 | Form: SPRAY
Manufacturer: Young Living Essential Oils, LC
Category: otc | Type: HUMAN OTC DRUG LABEL
Date: 20240916

ACTIVE INGREDIENTS: MENTHOL, UNSPECIFIED FORM 0.005 g/1 g
INACTIVE INGREDIENTS: DOCOSANOL; XANTHAN GUM; PICEA MARIANA LEAF OIL; GLYCERYL MONOCAPRYLATE; WATER; OLIVE OIL; GLYCERIN; HELIANTHUS ANNUUS SEED WAX; SAFFLOWER OIL; SUNFLOWER OIL; JOJOBA OIL; POLYGLYCERYL-10 PENTASTEARATE; EUROPEAN ELDERBERRY; SODIUM STEAROYL LACTYLATE; LAVENDER OIL; ALOE VERA LEAF; GLYCERYL MONOUNDECYLENATE; ANHYDROUS CITRIC ACID; HELICHRYSUM ITALICUM FLOWER OIL; PHYTATE SODIUM

Lavaderm After Sun

Active ingredient

Menthol 0.5%

Purpose

Topical analgesic

Uses

- For the temporary relief of pain and itching associated with minor burns, sunburn, minor cuts, scrapes, insect bites, and minor skin irritations

Warnings

For external use only

When using this product

- avoid contact with eyes

Stop use and ask a doctor if

- condition worsens
- symptoms last more than 7 days or clear up and occur again within a few days

Keep out of reach of children to avoid accidental ingestion. If swallowed, get medical help or contact a Poison Control Center right away.

Directions

Shake Well

Adults and children 2 years of age and older: apply to affected area not more than 3 to 4 times daily. Children under 2 years of age: ask a doctor

Other information

- store at controlled room temperature (68° to 77°F)

Inactive ingredients

Water, olive oil, glycerin, safflower oil, sunflower oil, jojoba oil, polyglyceryl-10 pentastearate, glyceryl monocaprylate, helianthus annuus seed wax, European elderberry, xanthan gum, docosanol, sodium stearoyl lactylate, lavender oil, aloe vera leaf, glyceryl monoundecylenate, phytate sodium, picea mariana leaf oil, helichrysum italicum flower oil, citric add

Questions or comments?

call 1-800-371-3515

Principal Display Panel

FOR PAIN & ITCH

SOOTHES & COOLS SKIN

IMMEDIATE RELIEF